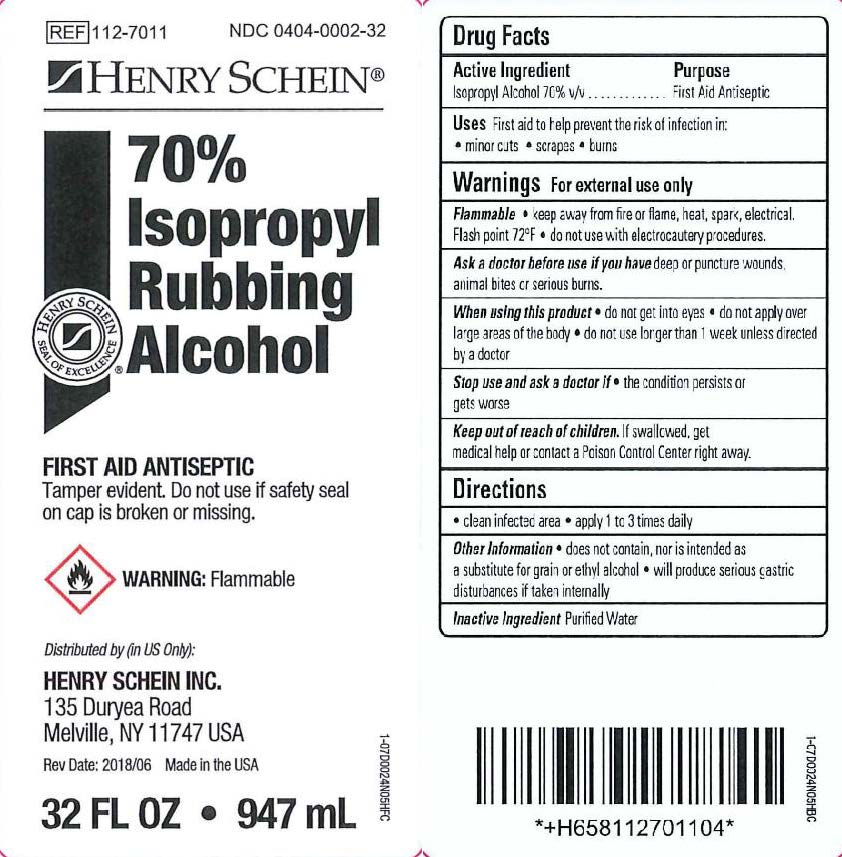 DRUG LABEL: Isopropyl Rubbing Alcohol
NDC: 0404-0002 | Form: SOLUTION
Manufacturer: Henry Schein Inc.
Category: otc | Type: HUMAN OTC DRUG LABEL
Date: 20241115

ACTIVE INGREDIENTS: ISOPROPYL ALCOHOL 700 mg/1 mL
INACTIVE INGREDIENTS: WATER

Isopropyl Rubbing Alcohol

Drug Facts

Active Ingredient

Isopropyl Alcohol 70% v/v

Purpose

First Aid Antiseptic

Uses

First aid to help prevent the risk of infection in:

- minor cuts
- scrapes
- burns

Warnings

For external use only

Flammable

- keep away from fire or flame, heat, spark, electrical. Flash point 72°F
- do not use with electrocautery procedures.

Ask a doctor before use if you havedeep or puncture wounds, animal bites or serious burns.

When using this product

- do not get into eyes
- do not apply over large areas of the body
- do not use longer than 1 week unless directed by a doctor

Stop use and ask a doctor if

- the condition persists or gets worse

Keep out of reach of children.In case of accidental ingestion, seek professional assistance or contact a Poison Control Center (1-800-222-1222) immediately.

Directions

- clean infected area
- apply small amount of this product on the area 1 to 3 times daily
- may be covered with a sterile bandage
- if bandaged, let dry first

Other Information

- store at room temperature
- does not contain, nor is intended as a substitute for grain or ethyl alcohol
- will produce serious gastric disturbances if taken internally

Inactive Ingredient

Purified Water

PRINCIPAL DISPLAY PANEL

Item # 112-7011
NDC 0404-0002-32

HENRY SCHEIN®

70% Isopropyl
Rubbing Alcohol

FIRST AID ANTISEPTICTamper evident cap for your protection. If ring-band
is detached from cap or missing do not use.

WARNING:Flammable

(manufacturer)

Distributed by (in US Only):

HENRY SCHEIN INC.
135 Duryea Road
Melville, NY 11747 USA

Rev Date: 05/14

Made in the USA

32 FL OZ • 946 mL